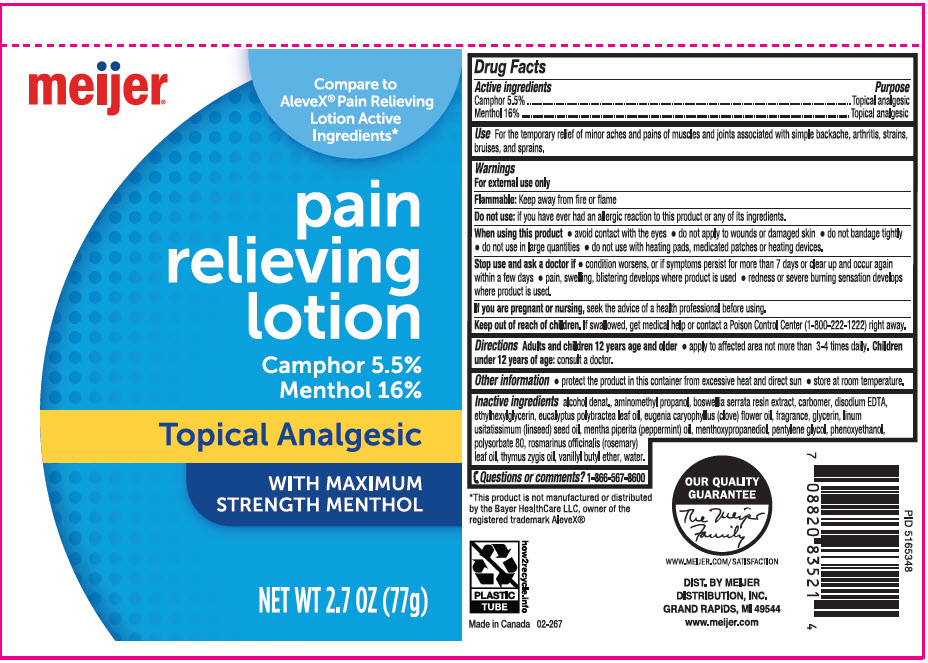 DRUG LABEL: Meijer Pain Relieving
NDC: 79481-0051 | Form: LOTION
Manufacturer: Meijer Distribution, Inc
Category: otc | Type: HUMAN OTC DRUG LABEL
Date: 20241115

ACTIVE INGREDIENTS: CAMPHOR (SYNTHETIC) 55 mg/1 g; MENTHOL, UNSPECIFIED FORM 160 mg/1 g
INACTIVE INGREDIENTS: ALCOHOL; AMINOMETHYLPROPANOL; INDIAN FRANKINCENSE; CARBOMER HOMOPOLYMER, UNSPECIFIED TYPE; EDETATE DISODIUM; Ethylhexylglycerin; Eucalyptus polybractea leaf oil; CLOVE OIL; GLYCERIN; LINSEED OIL; PEPPERMINT OIL; 3-((L-MENTHYL)OXY)PROPANE-1,2-DIOL; Pentylene glycol; Phenoxyethanol; Polysorbate 80; ROSEMARY OIL; SPANISH THYME OIL; Vanillyl butyl ether; Water

Meijer® Pain Relieving Lotion
Topical analgesic

Drug Facts

ACTIVE INGREDIENT

Active ingredient | Purpose
Camphor 5.5% | Topical analgesic
Menthol 16% | Topical analgesic

Use

For the temporary relief of minor aches and pains of muscles and joints associated with simple backache, arthritis, strains, bruises and sprains.

Warnings

For external use only

Flammable: Keep away from fire or flame

Do not use: if you ever had an allergic reaction to this product or any of its ingredients.

When using this product

- avoid contact with eyes
- do not apply to wounds or damaged skin
- do not bandage tightly
- do not use in large quantities
- do not use with heating pads, medicated patches or heating devices.

Stop use and ask a doctor if

- condition worsens, or if symptoms persist for more than 7 days or clear up and occur again within a few days
- pain, swelling, blistering develops where product is used
- redness or severe burning sensation develops where product is used.

PREGNANCY OR BREAST FEEDING

If you are pregnant or nursing, seek the advice of a health professional before using.

Keep out of reach of children. If swallowed, get medical help or contact a Poison Control Center (1-800-222-1222) right away.

Directions

Adults and children 12 years of age and older:

- apply to affected area not more than 3 to 4 times daily.

Children under 12 years of age: consult a doctor.

Other information

- protect the product in this container from excessive heat and direct sun
- store at room temperature.

Inactive ingredients

alcohol denat., aminomethyl propanol, boswellia serrata resin extract, carbomer, disodium EDTA, ethylhexylglycerin, eucalyptus polybractea leaf oil, Eugenia caryophyllus (clove) flower oil, fragrance, glycerin, linum ultatissimum (linseed) seed oil, mentha piperita (peppermint) oil, menthoxypropanediol, pentylene glycol, phenoxyethanol, polysorbate 80, rosmarinus officinalis (rosemary) leaf oil, thymus zygis oil, vanillyl butyl ether, water.

Questions or comments?

1-866-567-8600

DIST. BY MEIJER
DISTRIBUTION, INC.
GRAND RAPIDS, MI 49544

PRINCIPAL DISPLAY PANEL - 77 g Tube Label

meijer®

Compare to
AleveX® Pain Relieving
Lotion Active
Ingredients*

pain
relieving
lotion

Camphor 5.5%
Menthol 16%

Topical Analgesic

WITH MAXIMUM
STRENGTH MENTHOL

NET WT 2.7 OZ (77g)